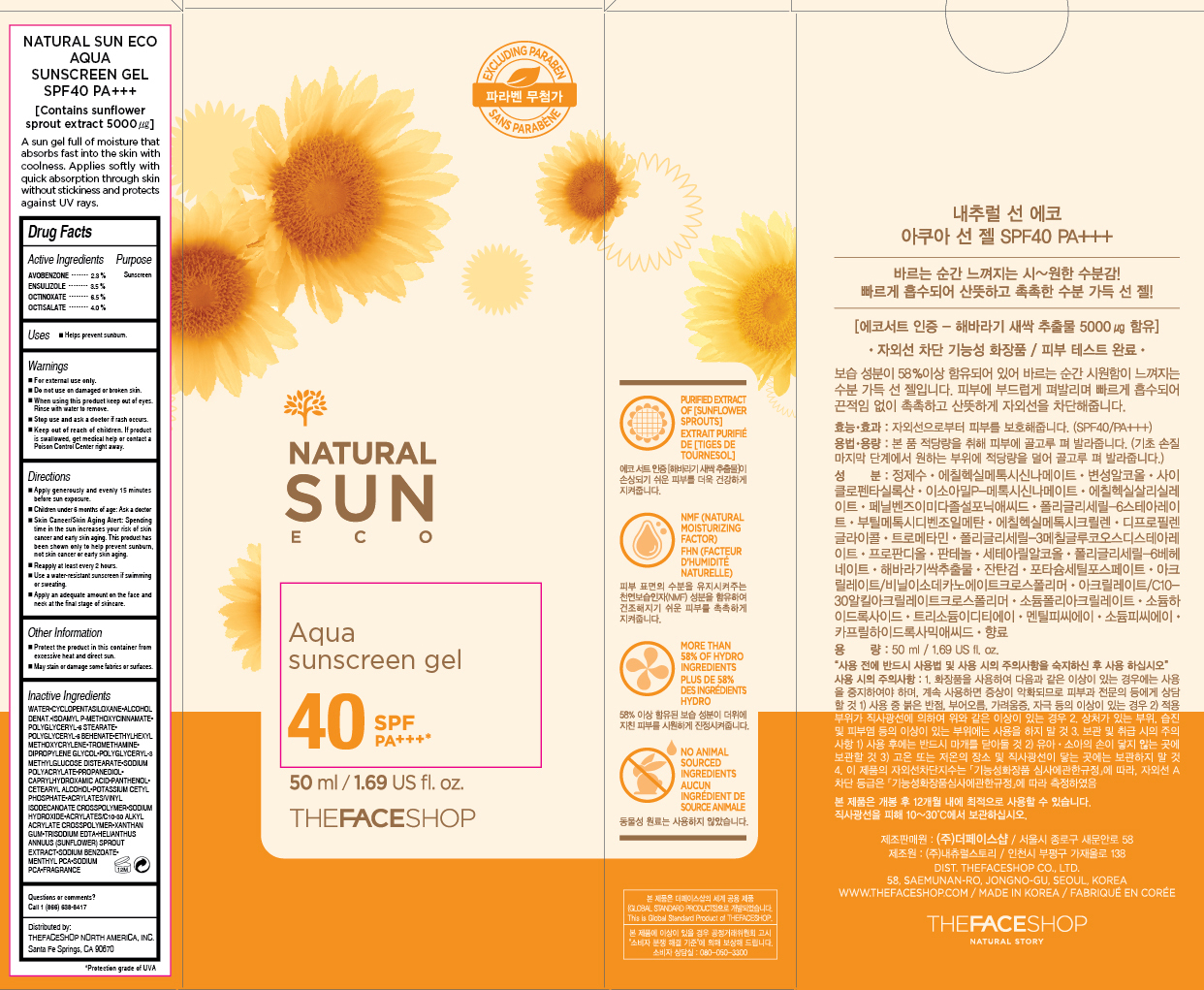 DRUG LABEL: NATURAL SUN ECO
NDC: 51523-176 | Form: GEL
Manufacturer: THEFACESHOP CO., LTD.
Category: otc | Type: HUMAN OTC DRUG LABEL
Date: 20151001

ACTIVE INGREDIENTS: AVOBENZONE 1.15 g/50 mL; ENSULIZOLE 1.75 g/50 mL; OCTINOXATE 3.25 g/50 mL; OCTISALATE 2 g/50 mL
INACTIVE INGREDIENTS: WATER

NATURAL SUN ECO Aqua Sunscreen Gel 40 SPF PA+++ 31500176

Active Ingredients

Avobenzone 2.3%
Ensulizole 3.5%
Octinoxate 6.5%
Octisalate 4.0%

Purpose

Sunscreen
Sunscreen
Sunscreen
Sunscreen

Uses

Helps prevent sunburn.

Warnings

For external use only.

Do not use on damaged or broken skin

When using this product keep out of eyes. Rinse with water to remove.

Stop use and ask a doctor if rash occurs.

Keep out of reach of children. If product is swallowed, get medical help or contact a Poison Control Center right away.

Directions

Apply generously and evenly 15 minutes before sun exposure.
Children under 6 months of age: Ask a doctor.
Skin Cancer/Skin Aging Alert: Spending time in the sun increases your risk of skin cancer and early skin aging. This product has been shown only to help prevent sunburn, not skin cancer or early skin aging.
Reapply at least every 2 hours.
Use a water-resistant sunscreen if swimming or sweating.

Apply an adequate amount on the face and neck at the final stage of skincare.

OTHER SAFETY INFORMATION

Protect the product in this container from excessive heat and direct sun.

May stain or damage some fabrics or surfaces.

Inactive Ingredients

WATER, CYCLOPENTASILOXANE, ALCOHOL DENAT., ISOAMYL P-METHOXYCINNAMATE, POLYGLYCERYL-6 STEARATE, POLYGLYCERYL-6 BEHENATE, ETHYLHEXYL METHOXYCRYLENE, TROMETHAMINE, DIPROPYLENE GLYCOL, POLYGLYCERYL-3 METHYLGLUCOSE DISTEARATE, SODIUM POLYACRYLATE, PROPANEDIOL, CAPRYLHYDROXAMIC ACID, PANTHENOL, CETEARYL ALCOHOL, POTASSIUM CETYL PHOSPHATE, ACRYLATES/VINYL ISODECANOATE CROSSPOLYMER, SODIUM HYDROXIDE, ACRYLATES/C10-30 ALKYL ACRYLATE CROSSPOLYMER, XANTHAN GUM, TRISODIUM EDTA, HELIANTHUS ANNUUS (SUNFLOWER) SPROUT EXTRACT, SODIUM BENZOATE, MENTHYL PCA, SODIUM PCA, FRAGRANCE

Questions or comments? Call 1-866-638-8417

Distributed by:

THEFACESHOP NORTH AMERICA, INC.

Santa Fe Springs, CA 90670

PACKAGE LABEL

NATURAL SUN ECO

Aqua Sunscreen Gel

SPF 40 PA+++

[Contains sunflower sprout extract 5000 µg

A sun gel full of moisture that absorbs fast into the skin with coolness.

Applies softly with quick abosorption through skin without stickiness and protects against UV rays.